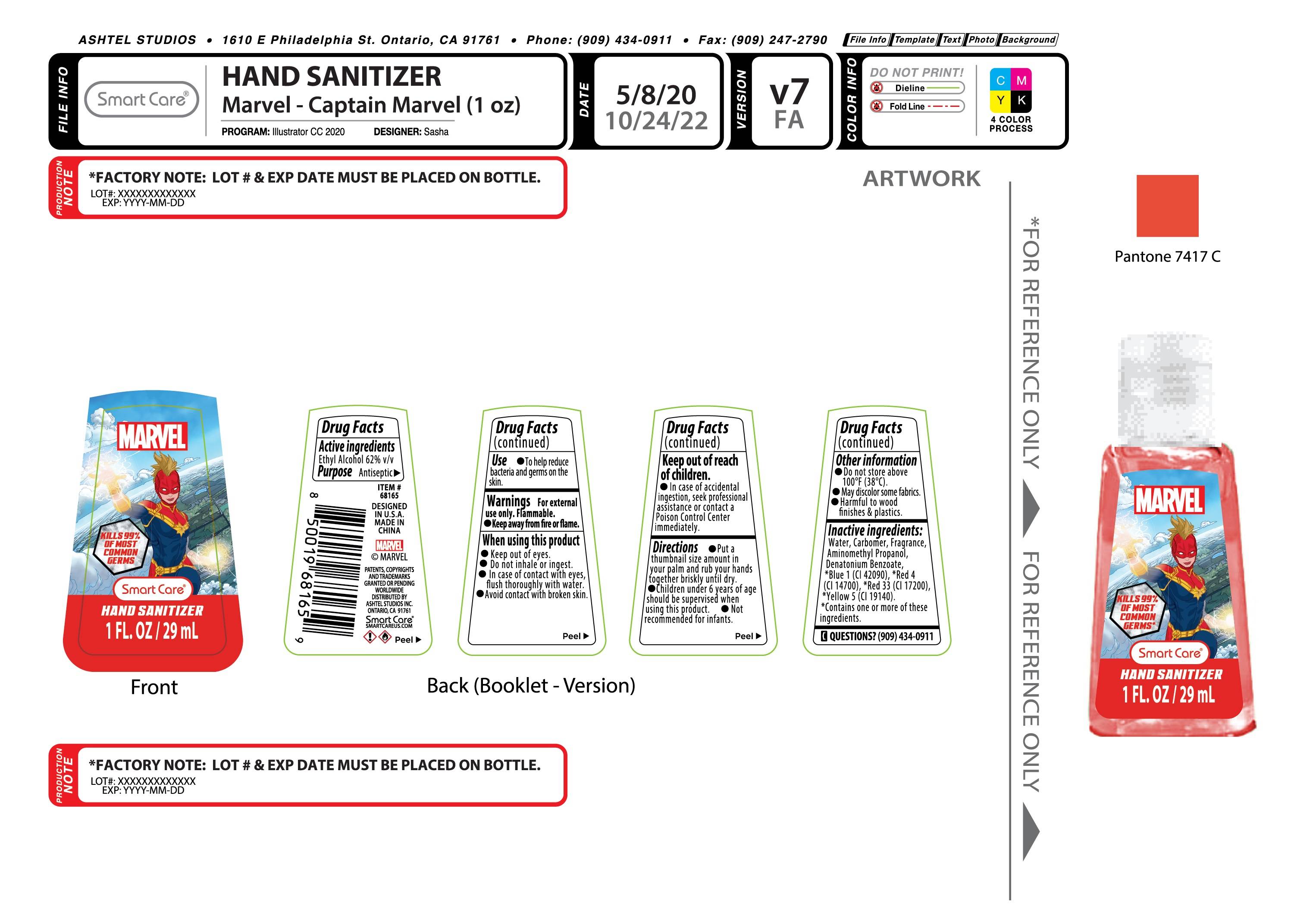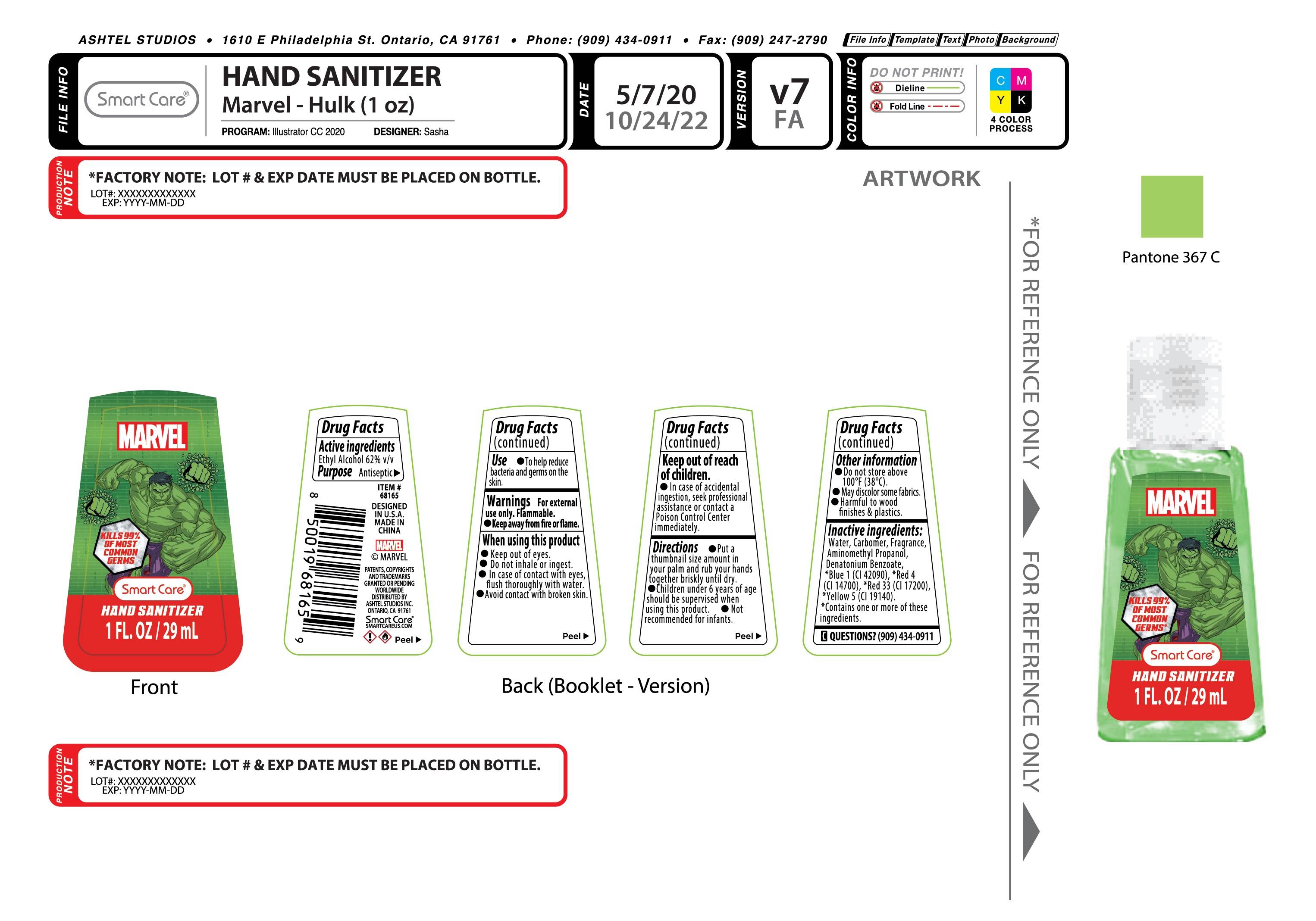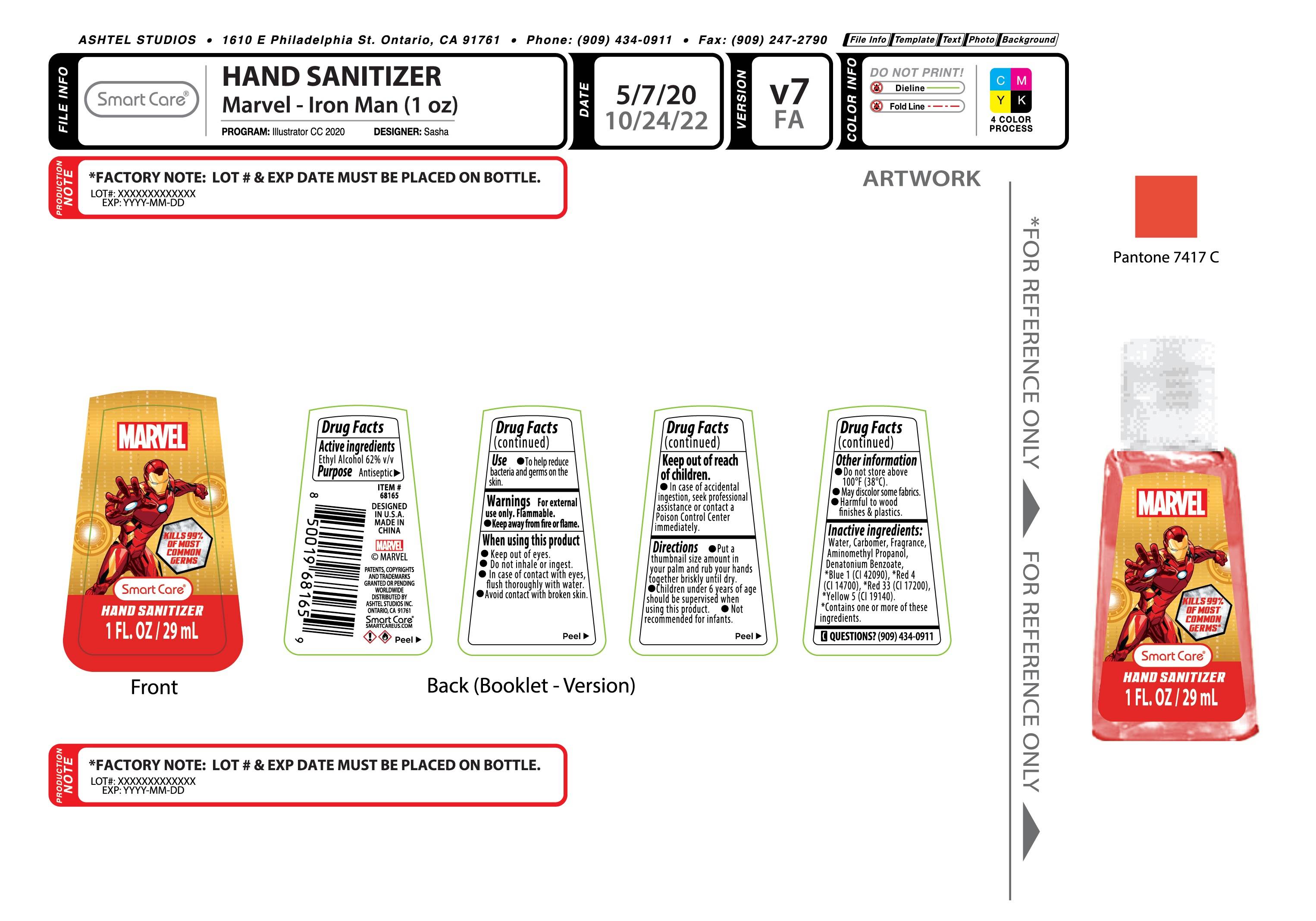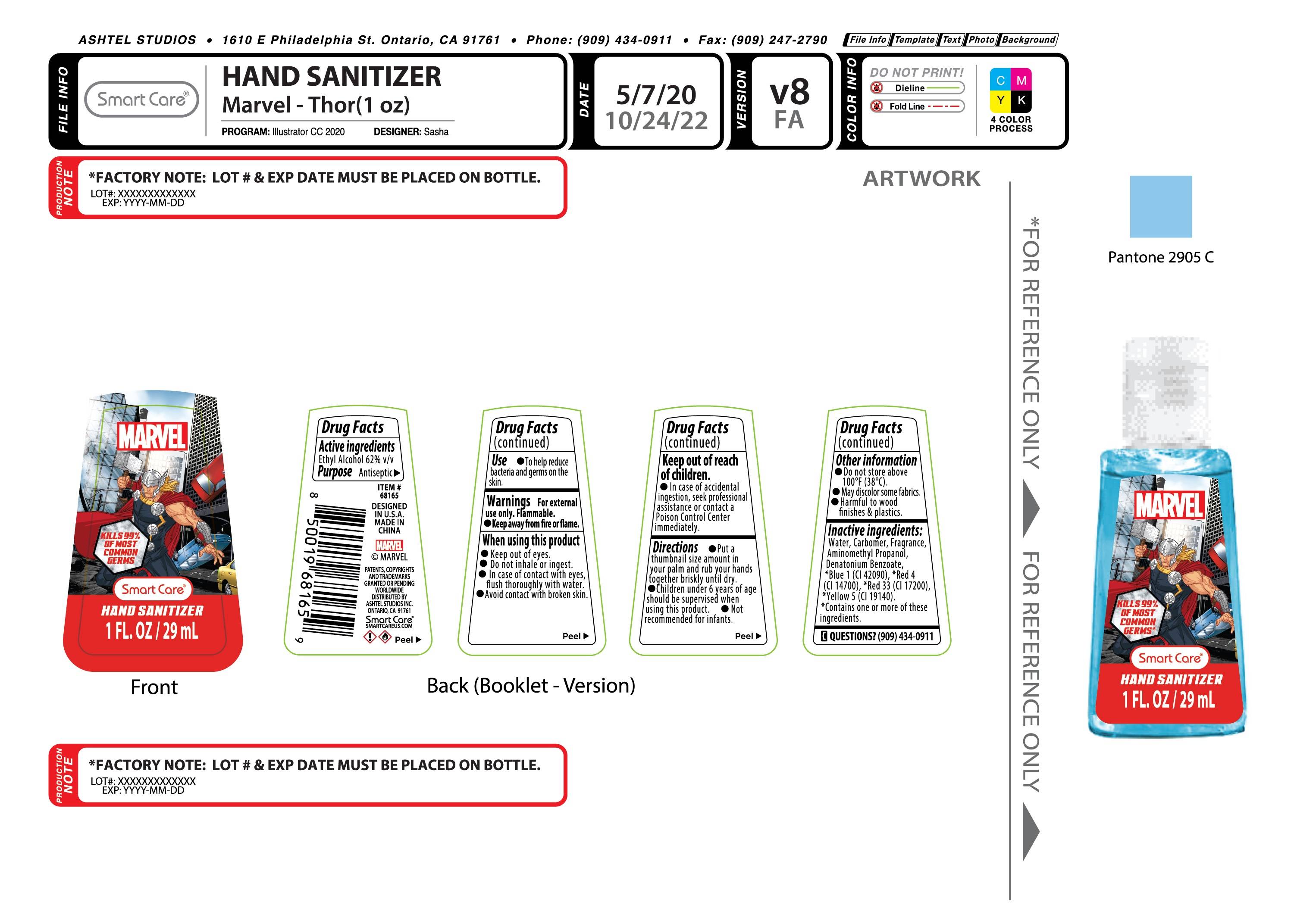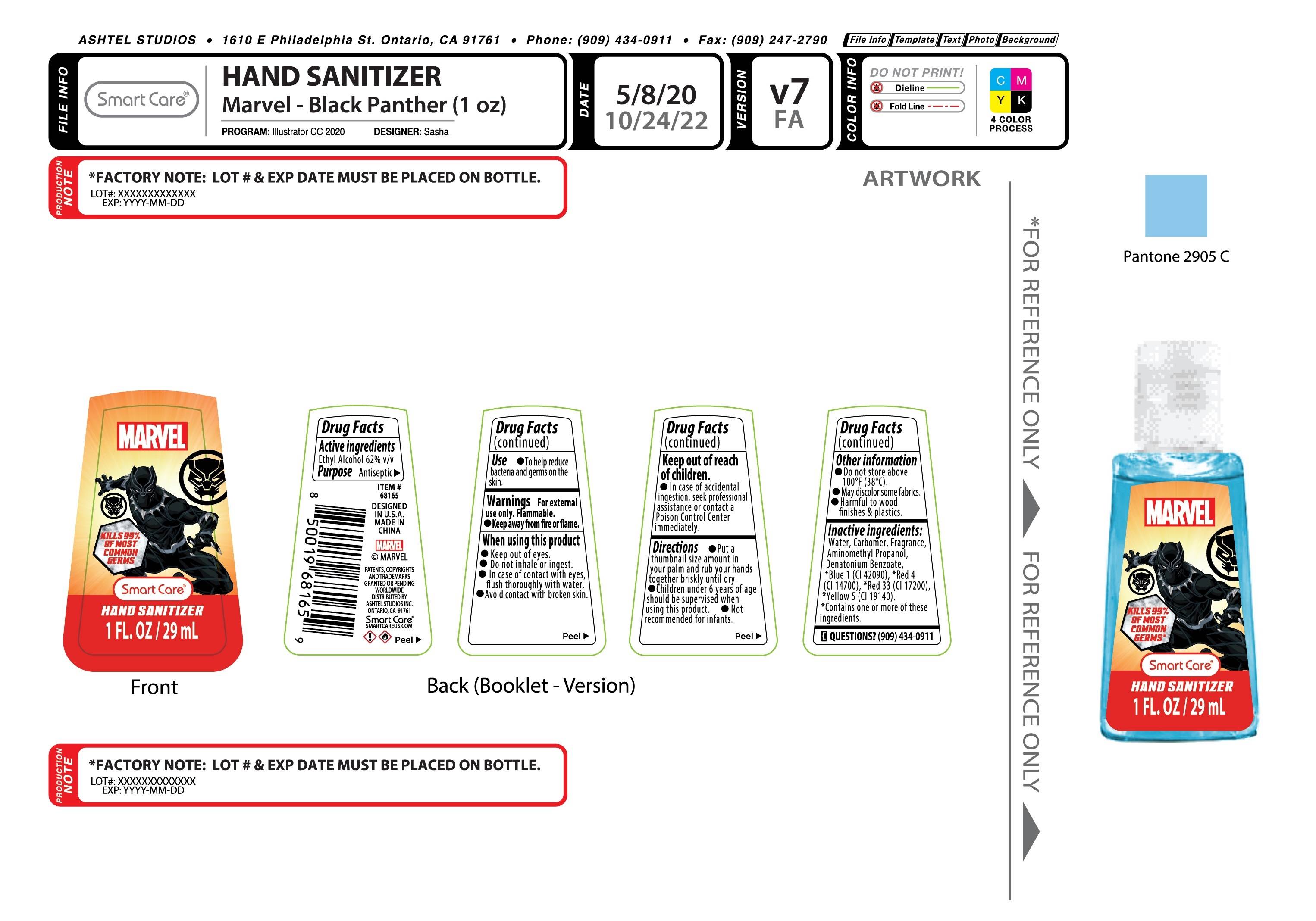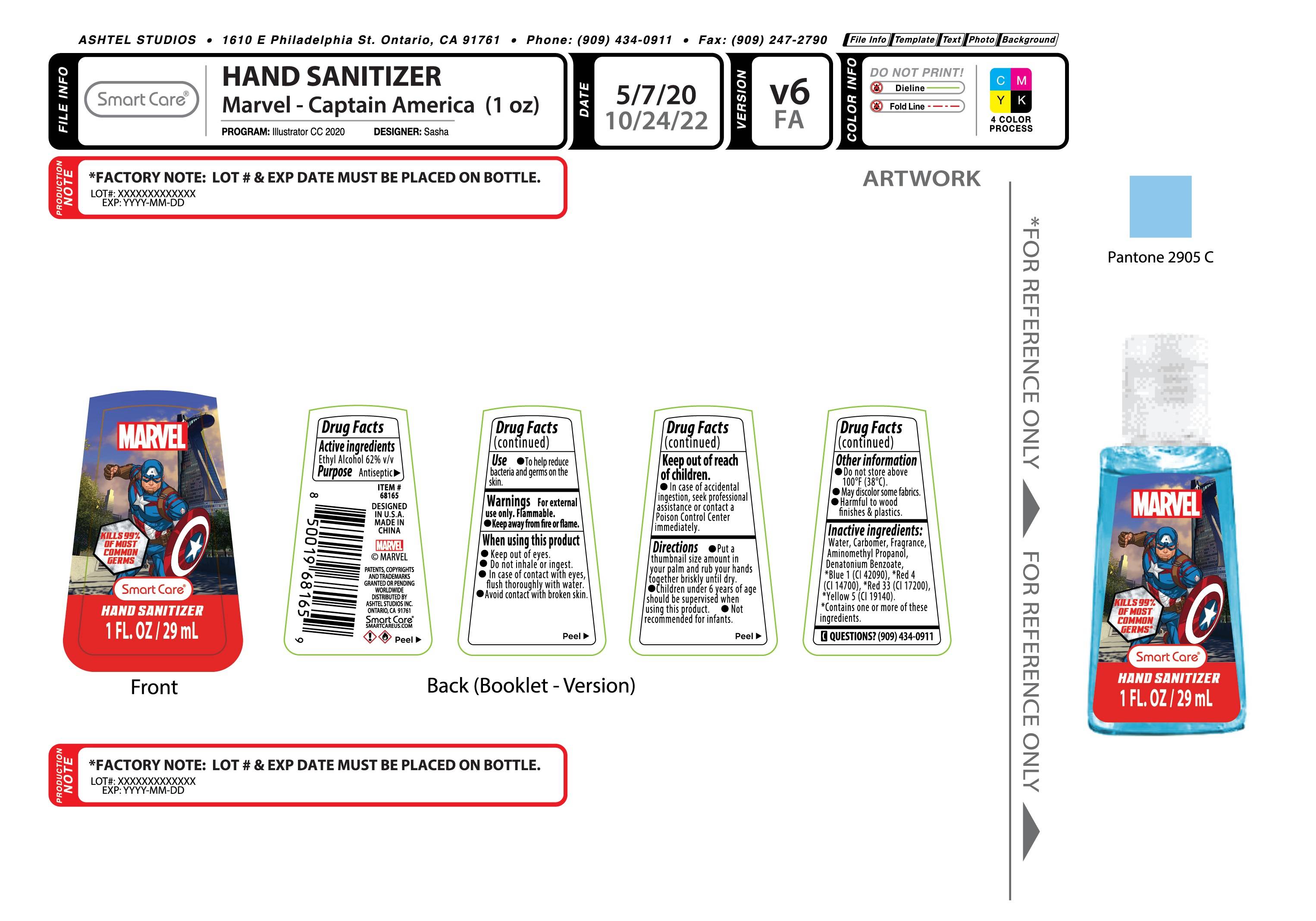 DRUG LABEL: Smart care Marvel Hand Sanitizer 1oz
NDC: 54860-406 | Form: LIQUID
Manufacturer: Shenzhen Lantern Scicence Co.,Ltd.
Category: otc | Type: HUMAN OTC DRUG LABEL
Date: 20230511

ACTIVE INGREDIENTS: ALCOHOL 62 mL/100 mL
INACTIVE INGREDIENTS: CARBOMER 940 0.3 mL/100 mL; AMINOMETHYLPROPANOL 0.12 mL/100 mL; WATER 37.3495 mL/100 mL; DENATONIUM BENZOATE 0.0005 mL/100 mL; FD&C RED NO. 4 0.01 mL/100 mL; D&C RED NO. 33 0.01 mL/100 mL; LATHYRUS ODORATUS SEED 0.2 mL/100 mL; FD&C YELLOW NO. 5 0.01 mL/100 mL; FD&C BLUE NO. 1 0.01 mL/100 mL

Marvel IronMan Hand Sanitizer

Drug facts

Active Ingredient

Active Ingredient Purpose

Ethyl Alcohol 62%（V/V） Antiseptic

Use

Hand sanitizer helps to reduce bacteria that potentially can cause disease.For use when soap and water are not available.

Use(s)

To help reduce bacteria and germs on the skin.

Warning

For external use only,Flammable,Keep away from heat or flame.

WARNINGS AND PRECAUTIONS

For external use only.

Flammable, keep away from heat and flame.

STOP USE

Discontinue if skin becomes irritated and ask a doctor .

Keep out of reach of children. In case of accidental ingestion, seek professional assistance or contact a poson control center immediately.

keep out of reach of children

In case of accidental ingestion,seek professional assistant or contact a Poison Control Center immediately.

DOSAGE AND ADMINISTRATION

Recommended for repeated use.

use anywhere without water.

Inactive ingredients

Water(Aqua),Carbomer,Fragrance, Aminomethyl Propanol,Denatonium Benzoate,Yellow 5,Red 4,,Red 33

Directions

Put a thumbnail size smount in your palm and rub your hands together briskly until dry.

Children under 6 years of age should be supervised when using this product

Not recommended for infants.

When using this product

keep out of eyes. In case of contact with eyes, flush thoroughly with water.

Do not inhale or ingest.

Avoid contact with broken skin.

Other information

Do not store above 105F.

May discolor some fabrics.

Harmful to wood finishes and plastics.

When using this product

Keep out of eyes,ears

Do not inhale or ingest.

In case of contact with eyes,flush thoroughly with water

Avoid contact with broken skin.

Other information

Do not store above 100℉（38℃）.

May discolor some fabrics.

Harmful to wood finishes&plastics.

Purpose

Antiseptic

Packaging

Drug facts